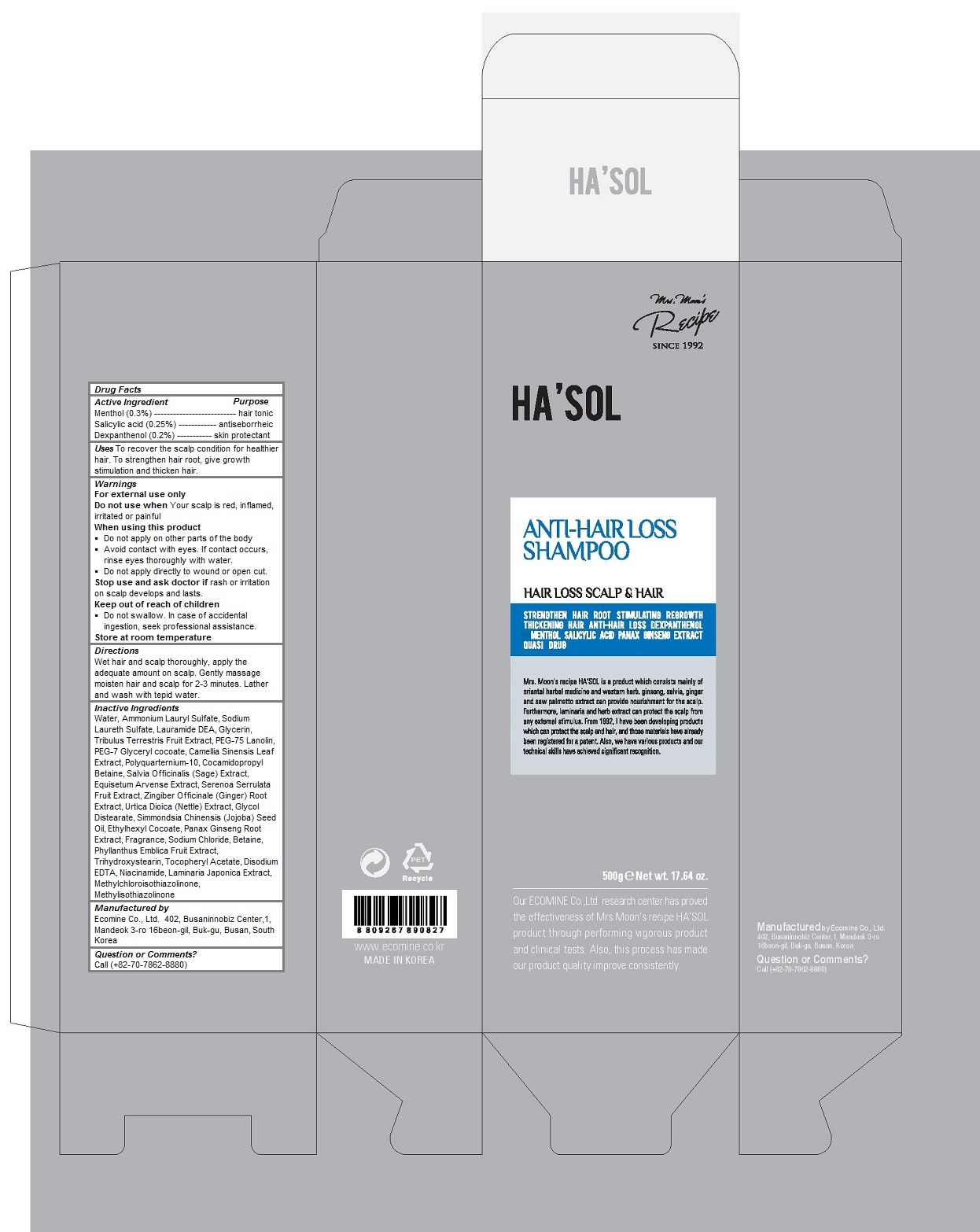 DRUG LABEL: HASOL Anti Hair Loss
NDC: 51270-124 | Form: SHAMPOO
Manufacturer: ECOMINE Co., Ltd.
Category: otc | Type: HUMAN OTC DRUG LABEL
Date: 20160331

ACTIVE INGREDIENTS: Dexpanthenol 0.002 1/500 g; Menthol 0.003 1/500 g; Salicylic Acid 0.0025 1/500 g
INACTIVE INGREDIENTS: water; Ammonium Lauryl Sulfate; Sodium Laureth Sulfate; LAURIC DIETHANOLAMIDE; Glycerin; TRIBULUS TERRESTRIS FRUIT; PEG-75 Lanolin; PEG-7 GLYCERYL COCOATE; GREEN TEA LEAF; Cocamidopropyl Betaine; SALVIA OFFICINALIS ROOT; EQUISETUM ARVENSE BRANCH; SAW PALMETTO; GINGER; URTICA DIOICA LEAF; Glycol Distearate; JOJOBA OIL; ETHYLHEXYL COCOATE; ASIAN GINSENG; Sodium Chloride; Betaine; PHYLLANTHUS EMBLICA FRUIT; Trihydroxystearin; .ALPHA.-TOCOPHEROL ACETATE; EDETATE DISODIUM; Niacinamide; LAMINARIA JAPONICA; METHYLCHLOROISOTHIAZOLINONE; Methylisothiazolinone

HA'SOL Anti-Hair Loss Shampoo

INDICATIONS AND USAGE

Uses To recover the scalp condition for healthier hair. To strengthen hair root, give growth stimulation and thicken hair.